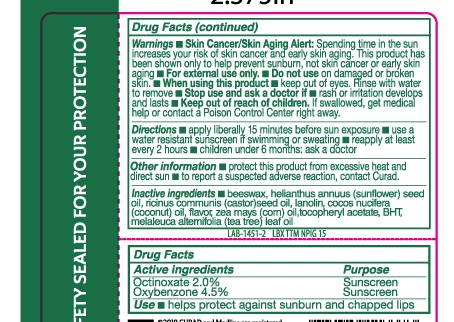 DRUG LABEL: Tea Tree Lip Balm, SPF 15
NDC: 63645-176 | Form: STICK
Manufacturer: OraLabs
Category: otc | Type: HUMAN OTC DRUG LABEL
Date: 20250428

ACTIVE INGREDIENTS: OCTINOXATE 20 mg/1 g; OXYBENZONE 45 mg/1 g
INACTIVE INGREDIENTS: SUNFLOWER OIL 304 mg/1 g; WHITE WAX 305 mg/1 g; ACETYLATED LANOLIN 97 mg/1 g

Drug Facts

Active ingredient

Octinoxate (2.0%), Oxybenzone (4.5%)

Purpose

Sunscreen

Keep Out of Reach of Children

If swallowed get medical help or contact a Poison Control Center right away.

Uses

Prevents Sunburns

Warnings

Skin Cancer/Skin Aging Alert: Spending time in the sun increases your risk of skin cancer and early skin aging. This product has been shown only to prevent sunburn, not skin cancer or early aging.

For external use only: Stop use and ask a doctor: if rash or irritation develops and lasts.

Directions

Apply liberally before sun exposure and as needed. Children under 6 months of age: Ask a doctor before use.

Inactive Ingredients

Synthetic Beeswax, Helianthus Annuus (Sunflower) Seed Oil, Ricinus Communis (Castor) Seed Oil, Lanolin, Cocos Nucifera (Coconut) Oil, Flavor, Zea Mays (Corn) Oil, Tocopheryl Acetate, BHT, Melaleuca Alternifolia (Tea Tree) Leaf Oil